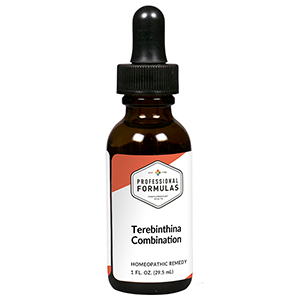 DRUG LABEL: Terebinthina Combination
NDC: 63083-9248 | Form: LIQUID
Manufacturer: Professional Complementary Health Formulas
Category: homeopathic | Type: HUMAN OTC DRUG LABEL
Date: 20190815

ACTIVE INGREDIENTS: APIS MELLIFERA 4 [hp_X]/29.5 mL; STRYCHNOS IGNATII SEED 4 [hp_X]/29.5 mL; SOLIDAGO VIRGAUREA FLOWERING TOP 4 [hp_X]/29.5 mL; VERATRUM ALBUM ROOT 4 [hp_X]/29.5 mL; BERBERIS VULGARIS ROOT BARK 6 [hp_X]/29.5 mL; PHOSPHORUS 6 [hp_X]/29.5 mL; TURPENTINE OIL 6 [hp_X]/29.5 mL; MERCURIC CHLORIDE 12 [hp_X]/29.5 mL
INACTIVE INGREDIENTS: ALCOHOL; WATER

R248

ACTIVE INGREDIENTS

Apis mellifica 4X
Ignatia amara 4X
Solidago virgaurea 4X
Veratrum album 4X
Berberis vulgaris 6X
Phosphorus 6X
Terebinthina 6X
Mercurius corrosivus 12X

QUESTIONS

Professional Formulas

PO Box 2034 Lake Oswego, OR 97035

INDICATIONS

For the temporary relief of diarrhea, mild abdominal or back pain, or urinary discomfort.*

PURPOSE

*Claims based on traditional homeopathic practice, not accepted medical evidence. Not FDA evaluated.

WARNINGS

Consult a doctor if condition worsens, if symptoms persist, or are accompanied by a fever, vomiting, or bloody or cloudy urine. Keep out of the reach of children. In case of overdose, get medical help or contact a poison control center right away. If pregnant or breastfeeding, ask a healthcare professional before use.

Keep out of the reach of children.

PREGNANCY OR BREAST FEEDING

If pregnant or breastfeeding, ask a healthcare professional before use.

DIRECTIONS

Place drops under tongue 30 minutes before/after meals. Adults and children 12 years and over: Take 10 drops up to 3 times per day. Consult a physician for use in children under 12 years of age.

OTHER INFORMATION

Tamper resistant. If seal is broken, do not use. After opening, close container tightly and store at room temperature away from heat.

INACTIVE INGREDIENTS

40% ethanol, purified water.

LABEL

Est 1985

Professional Formulas

Complementary Health

Terebinthina Combination

Homeopathic Remedy

1 FL. OZ. (29.5 mL)